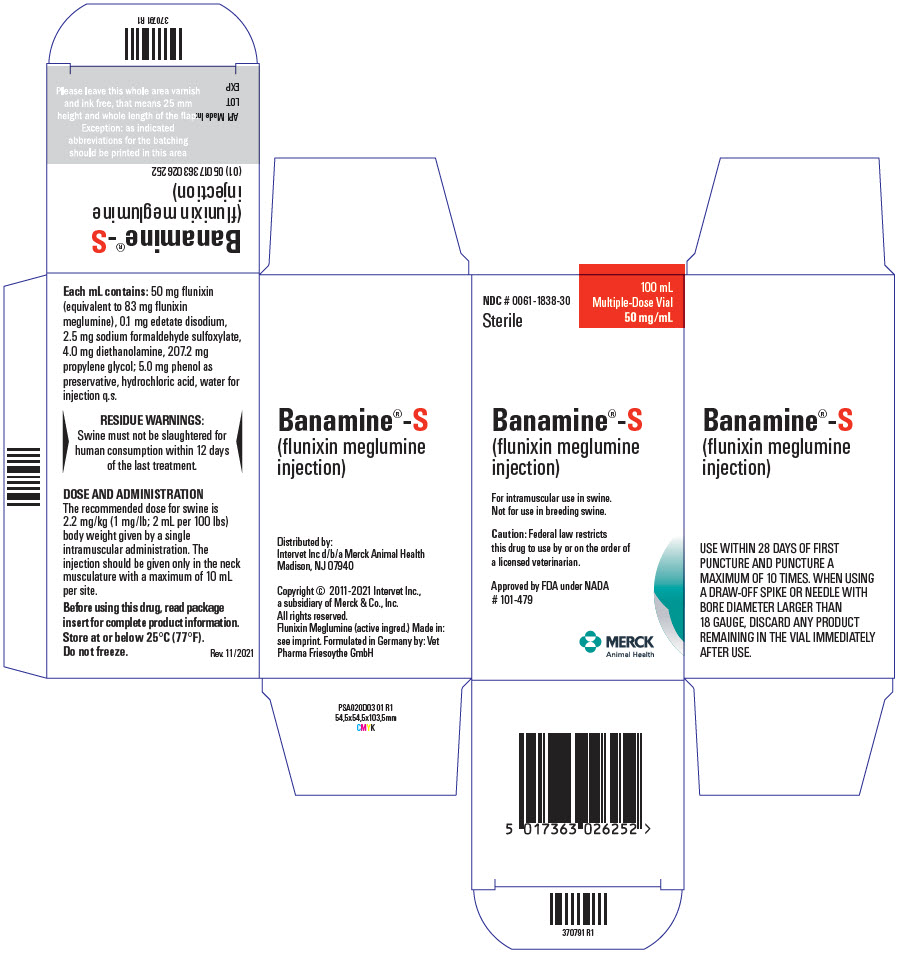 DRUG LABEL: Banamine-S
NDC: 0061-1838 | Form: INJECTION
Manufacturer: Merck Sharp & Dohme Corp.
Category: animal | Type: PRESCRIPTION ANIMAL DRUG LABEL
Date: 20241115

ACTIVE INGREDIENTS: FLUNIXIN 50 mg/1 mL

Banamine®-S
(flunixin meglumine injection)

50 mg/mL

For intramuscular use in swine.
Not for use in breeding swine.

PRODUCT
INFORMATION

Approved by FDA under NADA # 101-479

CAUTION

Federal law restricts this drug to use by or on the order of a licensed veterinarian.

DESCRIPTION

Each milliliter of BANAMINE-S (flunixin meglumine injection) contains 50 mg flunixin (equivalent to 83 mg flunixin meglumine), 0.1 mg edetate disodium, 2.5 mg sodium formaldehyde sulfoxylate, 4.0 mg diethanolamine, 207.2 mg propylene glycol; 5.0 mg phenol as preservative, hydrochloric acid, water for injection q.s.

CLINICAL PHARMACOLOGY

Flunixin meglumine is a potent non-narcotic, nonsteroidal, analgesic agent with anti-inflammatory and antipyretic activity. It is significantly more potent than pentazocine, meperidine, and codeine as an analgesic in the rat yeast paw test.

Flunixin is known to persist in inflammatory tissues^1 and is associated with anti-inflammatory properties which extend well beyond the period associated with detectable plasma drug concentrations^2. Therefore, prediction of drug concentrations based upon estimated plasma terminal elimination half-life will likely underestimate both the duration of drug action and the concentration of drug remaining at the site of activity.

The pharmacokinetic profiles were found to follow a 2-compartmental model, although a deep (third) compartment was observed in some animals. The mean terminal elimination half-life (β half-life) of flunixin after a single intramuscular injection of Banamine (2.2 mg/kg) to pigs was between 3 and 4 hours. The mean observed maximum plasma concentration was 2944 ng/mL, achieved at a mean time of approximately 0.4 hours. The mean AUC(0-LOQ) was 6431 ng*hr/mL. Following IM administration of flunixin, quantifiable drug concentration could be measured up to 18 hours post dose. The mean volume of distribution was 2003 mL/kg and the mean total clearance was 390 mL/hr/kg. The mean absolute bioavailability of flunixin following an intramuscular injection in the neck was 87%.

INDICATION

BANAMINE-S (flunixin meglumine injection) is indicated for the control of pyrexia associated with swine respiratory disease.

DOSE AND ADMINISTRATION

The recommended dose for swine is 2.2 mg/kg (1 mg/lb; 2 mL per 100 lbs) body weight given by a single intramuscular administration. The injection should be given only in the neck musculature with a maximum of 10 mL per site.

USE WITHIN 28 DAYS OF FIRST PUNCTURE AND PUNCTURE A MAXIMUM OF 10 TIMES. WHEN USING A DRAW-OFF SPIKE OR NEEDLE WITH BORE DIAMETER LARGER THAN 18 GAUGE, DISCARD ANY PRODUCT REMAINING IN THE VIAL IMMEDIATELY AFTER USE.

Note: Intramuscular injection may cause local tissue irritation and damage. In an injection-site irritation study, the tissue damage did not resolve in all animals by Day 28 post-injection. This may result in trim loss of edible tissue at slaughter.

CONTRAINDICATIONS

There are no known contraindications to this drug in swine when used as directed. Do not use in animals showing hypersensitivity to flunixin meglumine. Use judiciously when renal impairment or gastric ulceration is suspected.

RESIDUE WARNINGS

Swine must not be slaughtered for human consumption within 12 days of the last treatment.

PRECAUTIONS

As a class, cyclo-oxygenase inhibitory NSAIDs may be associated with gastrointestinal, renal and hepatic toxicity. Sensitivity to drug-associated adverse events varies with the individual patient. Patients at greatest risk for adverse events are those that are dehydrated, on concomitant diuretic therapy, or those with existing renal, cardiovascular, and/or hepatic dysfunction. Concurrent administration of potentially nephrotoxic drugs should be carefully approached. NSAIDs may inhibit the prostaglandins that maintain normal homeostatic function. Such prostaglandin effects may result in clinically significant disease in patients with underlying or pre-existing disease that has not been previously diagnosed.

Since many NSAIDs possess the potential to produce gastrointestinal ulceration, concomitant use of flunixin meglumine with other anti-inflammatory drugs, such as other NSAIDs and corticosteroids, should be avoided.

Not for use in breeding swine. The reproductive effects of BANAMINE-S (flunixin meglumine injection) have not been investigated in this class of swine.

Intramuscular injection may cause local tissue irritation and damage. In an injection site irritation study, the tissue damage did not resolve in all animals by Day 28 post-injection. This may result in trim loss of edible tissue at slaughter.

ADVERSE REACTIONS

Flunixin was mildly irritating at the injection sites. No other flunixin-related changes (adverse reactions) were noted in swine administered a 1× (2.2 mg/kg; 1.0 mg/lb) dose for 9 days.

ANIMAL SAFETY

Minimal toxicity manifested itself as statistically significant increased spleen weight at elevated doses (5× or higher daily for 9 days) with no change in normal microscopic architecture.

HOW SUPPLIED

BANAMINE-S (flunixin meglumine injection), 50 mg/mL is available in 100-mL (NDC # 0061-1838-30) multi-dose vials.

STORAGE AND HANDLING

Store at or below 25°C (77°F). Do not freeze. See the In-Use statement as provided in the Dose and Administration section.

REFERENCES

1. Lees P, Higgins AJ. Flunixin inhibits prostaglandin E2 production in equine inflammation. Res Vet Sci. 1984; 37:347-349.

2. Odensvik K. Pharmacokinetics of flunixin and its effect on prostaglandin F2α metabolite concentrations after oral and intravenous administration in heifers. J Vet Pharmacol Ther. 1995; 18:254-259.

Distributed by:
Intervet Inc d/b/a Merck Animal Health
Madison, NJ 07940

Copyright © 2011-2021 Intervet Inc., a subsidiary of Merck & Co., Inc.
All rights reserved.

Formulated in Germany by: Vet Pharma Friesoythe GmbH
Rev. 11/2021

368569 R1

PRINCIPAL DISPLAY PANEL - 100 mL Vial Carton

NDC # 0061-1838-30
Sterile

100 mL
Multiple-Dose Vial
50 mg/mL

Banamine®-S
(flunixin meglumine
injection)

For intramuscular use in swine.
Not for use in breeding swine.

Caution: Federal law restricts
this drug to use by or on the order of
a licensed veterinarian.

Approved by FDA under NADA
# 101-479

MERCK
Animal Health